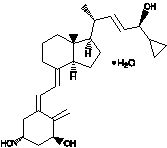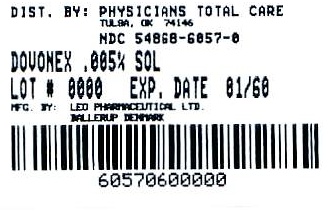 DRUG LABEL: Dovonex
NDC: 54868-6057 | Form: SOLUTION
Manufacturer: Physicians Total Care, Inc.
Category: prescription | Type: HUMAN PRESCRIPTION DRUG LABEL
Date: 20090914

ACTIVE INGREDIENTS: CALCIPOTRIENE 0.05 mg/1 mL
INACTIVE INGREDIENTS: HYDROXYPROPYL CELLULOSE; DIISOPROPANOLAMINE; MENTHOL; PROPYLENE GLYCOL; SODIUM CITRATE; WATER

Rx only
FOR TOPICAL DERMATOLOGIC USE ONLY.
Not for Ophthalmic, Oral or Intravaginal Use.

DESCRIPTION

Dovonex® (calcipotriene solution) Scalp Solution, 0.005% is a colorless topical solution containing calcipotriene monohydrate, a synthetic vitamin D3 derivative, for topical dermatologic use.

Chemically, calcipotriene monohydrate is (5Z,7E,22E,24S)-24-cyclopropyl-9,10-secochola-5,7,10(19),22-tetraene-1α,3β,24-triol monohydrate, with the empirical formula C27H40O3·H2O, a molecular weight of 430.6, and the following structural formula:

Calcipotriene monohydrate is a white or off-white crystalline substance. Dovonex® Scalp Solution contains calcipotriene monohydrate equivalent to 50 μg/g anhydrous calcipotriene in a vehicle of isopropanol (51% v/v), propylene glycol, hydroxypropyl cellulose, sodium citrate, menthol and water.

CLINICAL PHARMACOLOGY

In humans, the natural supply of vitamin D depends mainly on exposure to the ultraviolet rays of the sun for conversion of 7-dehydrocholesterol to vitamin D3 (cholecalciferol) in the skin. Calcipotriene is a synthetic analog of vitamin D3.

Although the precise mechanism of calcipotriene’s antipsoriatic action is not fully understood, in vitro evidence suggests that calcipotriene is roughly equipotent to the natural vitamin in its effects on proliferation and differentiation of a variety of cell types. Calcipotriene has also been shown, in animal studies, to be 100-200 times less potent in its effects on calcium utilization than the natural hormone.

Clinical studies with radiolabelled calcipotriene solution indicate that less than 1% of the applied dose of calcipotriene is absorbed through the scalp when the solution (2.0 mL) is applied topically to normal skin or psoriasis plaques (160 cm^2) for 12 hours, and that much of the absorbed calcipotriene is converted to inactive metabolites within 24 hours of application.

Vitamin D and its metabolites are transported in the blood, bound to specific plasma proteins. The active form of the vitamin, 1,25-dihydroxy vitamin D3 (calcitriol), is known to be recycled via the liver and excreted in the bile. Calcipotriene metabolism following systemic uptake is rapid, and occurs via a similar pathway to the natural hormone. The primary metabolites are much less potent than the parent compound.

There is evidence that maternal 1,25-dihydroxy vitamin D3 (calcitriol) may enter the fetal circulation, but it is not known whether it is excreted in human milk. The systemic disposition of calcipotriene is expected to be similar to that of the naturally occurring vitamin.

CLINICAL STUDIES

Adequate and well-controlled trials of patients treated with Dovonex® Scalp Solution, 0.005%, have demonstrated improvement usually beginning after 2 weeks of therapy. This improvement continued with approximately 31% of patients appearing either cleared (14%) or almost cleared (17%) after 8 weeks of therapy.

INDICATIONS AND USAGE

Dovonex® (calcipotriene solution) Scalp Solution, 0.005%, is indicated for the topical treatment of chronic, moderately severe psoriasis of the scalp. The safety and effectiveness of topical calcipotriene in dermatoses other than psoriasis have not been established.

CONTRAINDICATIONS

Dovonex® Scalp Solution, 0.005%, is contraindicated in those patients with acute psoriatic eruptions or a history of hypersensitivity to any of the components of the preparation. It should not be used by patients with demonstrated hypercalcemia or evidence of vitamin D toxicity.

WARNINGS

Avoid contact with the eyes or mucous membranes. Discontinue use if a sensitivity reaction occurs or if excessive irritation develops on uninvolved skin areas.

Drug product is flammable. Keep away from open flame.

PRECUATIONS

General

Use of Dovonex® Scalp Solution, 0.005%, may cause transient irritation of both lesions and surrounding uninvolved skin. If irritation develops, Dovonex® Scalp Solution, 0.005%, should be discontinued.

For external use only. Keep out of the reach of children. Always wash hands thoroughly after use.

Reversible elevation of serum calcium has occurred with use of topical calcipotriene. If elevation in serum calcium outside the normal range should occur, discontinue treatment until normal calcium levels are restored.

Information for Patients

Patients using Dovonex® Scalp Solution, 0.005%, should receive the following information and instructions:

1. This medication is to be used only as directed by the physician. It is for external use only. Avoid contact with the face or eyes. As with any topical medication, patients should wash their hands after application.
2. This medication should not be used for any disorder other than that for which it was prescribed.
3. Patients should report to their physician any signs of adverse reactions.
4. Patients that apply Dovonex® to exposed portions of the body should avoid excessive exposure to either natural or artificial sunlight (including tanning booths, sun lamps, etc.).

Carcinogenesis, Mutagenesis, Impairment of Fertility

When calcipotriene was applied topically to mice for up to 24 months at dosages of 3, 10 and 30 μg/kg/day (corresponding to 9, 30 and 90 μg/m^2/day), no significant changes in tumor incidence were observed when compared to control. In a study in which albino hairless mice were exposed to both UVR and topically applied calcipotriene, a reduction in the time required for UVR to induce the formation of skin tumors was observed (statistically significant in males only), suggesting that calcipotriene may enhance the effect of UVR to induce skin tumors. Patients that apply Dovonex® to exposed portions of the body should avoid excessive exposure to either natural or artificial sunlight (including tanning booths, sun lamps, etc.). Physicians may wish to limit or avoid use of phototherapy in patients that use Dovonex®.

Calcipotriene did not elicit any mutagenic effects in an Ames mutagenicity assay, a mouse lymphoma TK locus assay, a human lymphocyte chromosome aberration assay, or in a micronucleus assay conducted in mice.

Studies in rats at doses up to 54 μg/kg/day (324 μg/m^2/day) of calcipotriene indicated no impairment of fertility or general reproductive performance.

PregnancyTeratogenic Effects: Pregnancy Category C

Studies of teratogenicity were done by the oral route where bioavailability is expected to be approximately 40-60% of the administered dose. Increased rabbit maternal and fetal toxicity was noted at 12 μg/kg/day (132 μg/m^2/day). Rabbits administered 36 μg/kg/day (396 μg/m^2/day) resulted in fetuses with a significant increase in the incidences of pubic bones, forelimb phalanges, and incomplete bone ossification. In a rat study, oral doses of 54 μg/kg/day (318 μg/m^2/day) resulted in a significantly higher incidence of skeletal abnormalities consisting primarily of enlarged fontanelles and extra ribs. The enlarged fontanelles are most likely due to calcipotriene's effect upon calcium metabolism. The maternal and fetal calculated no-effect exposures in the rat (43.2 μg/m^2/day) and rabbit (17.6 μg/m^2/day) studies are greater than the expected human systemic exposure level (0.13 μg/m^2/day) from dermal application. There are no adequate and well-controlled studies in pregnant women. Therefore, Dovonex® Scalp Solution, 0.005%, should be used during pregnancy only if the potential benefit justifies the potential risk to the fetus.

Nursing Mothers

There is evidence that maternal 1,25-dihydroxy vitamin D3 (calcitriol) may enter the fetal circulation, but it is not known whether it is excreted in human milk. The systemic disposition of calcipotriene is expected to be similar to that of the naturally occurring vitamin. Because many drugs are excreted in human milk, caution should be exercised when Dovonex® (calcipotriene solution) Scalp Solution, 0.005%, is administered to a nursing woman.

Pediatric Use

Safety and effectiveness of Dovonex® Scalp Solution, 0.005%, in pediatric patients have not been specifically established. Because of a higher ratio of skin surface area to body mass, pediatric patients are at greater risk than adults of systemic adverse effects when they are treated with topical medication.

Geriatric Use

Of the total number of patients in clinical studies of calcipotriene solution, approximately 16% were 65 or older, while approximately 4% were 75 and over. The results of an analysis of severity of skin-related adverse events showed no differences for subjects over 65 years compared to those under 65 years, but greater sensitivity of some older individuals cannot be ruled out.

ADVERSE REACTIONS

In controlled clinical trials, the most frequent adverse reactions reported to be related to Dovonex® Scalp Solution, 0.005%, use were transient burning, stinging and tingling, which occurred in approximately 23% of patients. Rash was reported in about 11% of patients. Dry skin, irritation and worsening of psoriasis were reported in 1-5% of patients. Skin atrophy, hyperpigmentation, hypercalcemia, and folliculitis were not observed in these studies, but cannot be excluded.

OVERDOSAGE

Topically applied calcipotriene can be absorbed in sufficient amounts to produce systemic effects. Elevated serum calcium has been observed with excessive use of topical calcipotriene. If elevation in serum calcium should occur, discontinue treatment until normal calcium levels are restored. (See PRECAUTIONS.)

DOSAGE AND ADMINISTRATION

Comb the hair to remove scaly debris and after suitably parting, apply Dovonex® Scalp Solution, 0.005%, twice daily, only to the lesions, and rub in gently and completely, taking care to prevent the solution spreading onto the forehead. The safety and efficacy of Dovonex® Scalp Solution, 0.005%, have been demonstrated in patients treated for eight weeks.

Keep Dovonex® Scalp Solution, 0.005%, well away from the eyes. Avoid application of the solution to uninvolved scalp margins. Always wash hands thoroughly after use.

HOW SUPPLIED

Dovonex® (calcipotriene solution) Scalp Solution, 0.005% is available in 60 mL plastic bottles, NDC 54868-6057-0

STORAGE

Store at controlled room temperature 15° C - 25° C (59° F - 77° F). Avoid sunlight. Do not freeze.

PRINCIPAL DISPLAY PANEL

Dovonex® (calcipotriene solution) Scalp Solution, 0.005%